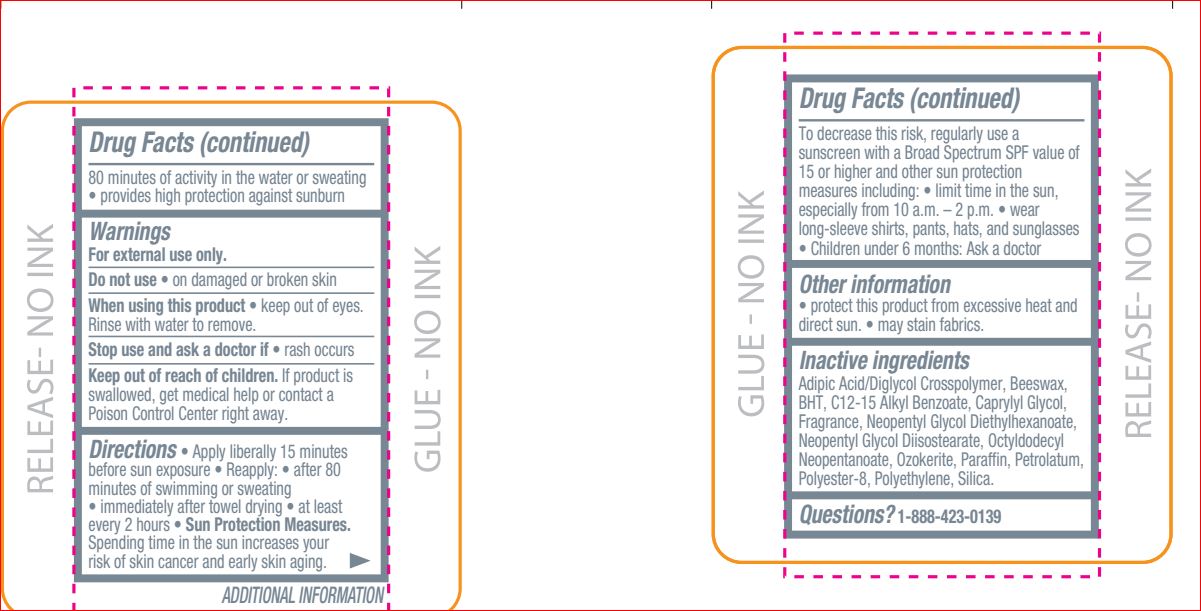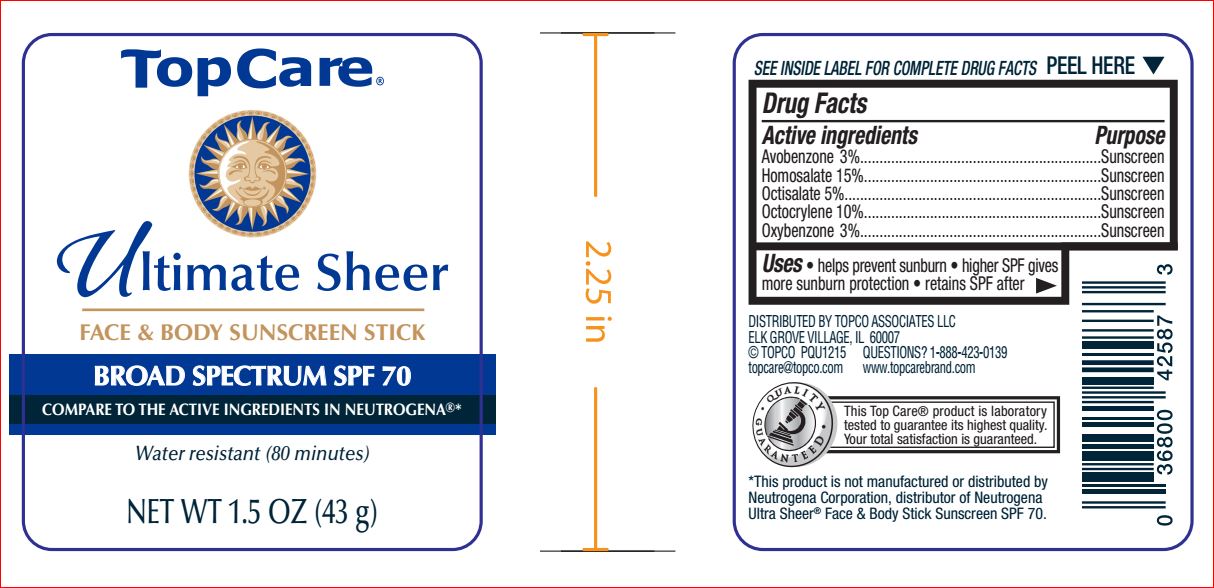 DRUG LABEL: Ultimate Sheer SPF 70
NDC: 36800-736 | Form: STICK
Manufacturer: Top Care
Category: otc | Type: HUMAN OTC DRUG LABEL
Date: 20180719

ACTIVE INGREDIENTS: Avobenzone 3 g/100 g; Homosalate 15 g/100 g; Octisalate 5 g/100 g; Octocrylene 10 g/100 g; Oxybenzone 3 g/100 g
INACTIVE INGREDIENTS: YELLOW WAX; BUTYLATED HYDROXYTOLUENE; ALKYL (C12-15) BENZOATE; Caprylyl Glycol; NEOPENTYL GLYCOL DIETHYLHEXANOATE; Neopentyl Glycol Diisostearate; Octyldodecyl Neopentanoate; CERESIN; Paraffin; Petrolatum; POLYESTER-8 (1400 MW, CYANODIPHENYLPROPENOYL CAPPED); HIGH DENSITY POLYETHYLENE; SILICON DIOXIDE

Drug Facts

Active ingredient Purpose
Avobenzone-3%
Homosalate-15% Sunscreen
Octisalate-5%
Octocrylene-10%
Oxybenzone-3%

INDICATIONS AND USAGE

Uses Helps prevent sunburn

Warnings For external use only.
Do not use on damaged or broken skin
When using this product keep out of eyes.
Rinse with water to remove.
Stop use and ask a doctor if rash occurs

Keep out of reach of children. If product is swallowed, get medical help or contact a Poison Control Center right away.

Directions

Remove cap and twist up tube.
See important warnings under "When using this
product" • apply liberally 15 minutes before sun
exposure • reapply:
• after 80 minutes of swimming or sweating
• immediately after towel drying
• at least every 2 hours
• Sun Protection Measures. Spending time in
the sun increases your risk of skin cancer and
early skin aging. To decrease this risk,

egularly use a sunscreen with a broad spectrum
SPF of 15 or higher and other sun protection
measures including: • limit time in the sun,
especially from 10 a.m. – 2 p.m. • wear
long-sleeve shirts, pants, hats, and sunglasses
• children under 6 months: Ask a doctor

Inactive ingredients Adipic Acid/Diglycol Crosspolymer, Beeswax,
BHT, C12-15 Alkyl Benzoate, Caprylyl Glycol,
Fragrance, Neopentyl Glycol Diethylhexanoate,
Neopentyl Glycol Diisostearate, Octyldodecyl
Neopentanoate, Ozokerite, Paraffin, Petrolatum,
Polyester-8, Polyethylene, Silica.

QUESTIONS?

1-888-423-0139